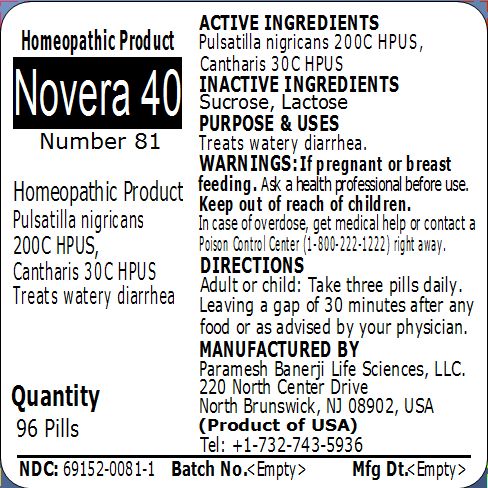 DRUG LABEL: Novera 40 Number 81
NDC: 69152-0081 | Form: PELLET
Manufacturer: Paramesh Banerji Life Sciences LLC
Category: homeopathic | Type: HUMAN OTC DRUG LABEL
Date: 20150317

ACTIVE INGREDIENTS: PULSATILLA PRATENSIS 200 [hp_C]/1 1; LYTTA VESICATORIA 30 [hp_C]/1 1
INACTIVE INGREDIENTS: SUCROSE; LACTOSE

Active Ingredients

Pulsatilla nigricans 200C HPUS, Cantharis 30C HPUS

Inactive Ingredients

Sucrose, Lactose

Purpose

Treats watery diarrhea

Uses

Treats watery diarrhea

Warnings

If pregnant or breast feeding ask a health professional before use.

Keep out of reach of children. In case of overdose, get medical help or contact a Poison Control Center (1-800-222-1222) right away.

Direction

Adult or child: Take three pills daily. Leaving a gap of 30 minutes after any food or as advised by your physician.

Manufactured by

Paramesh Banerji Life Sciences, LLC

220 North Center Drive

North Brunswick, NJ 08902, USA

Product of USA

Tel: +1-732-743-5936

Principal Display Panel

Homeopathic Product

Novera 40

Number 81

Homeopathic Product

Pulsatilla nigricans 200C HPUS, Cantharis 30C HPUS

Treats watery diarrhea

Quantity

96 Pills